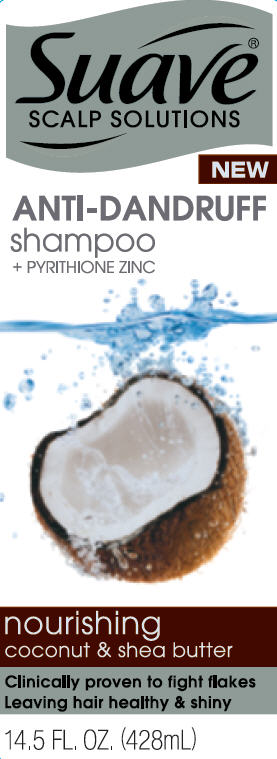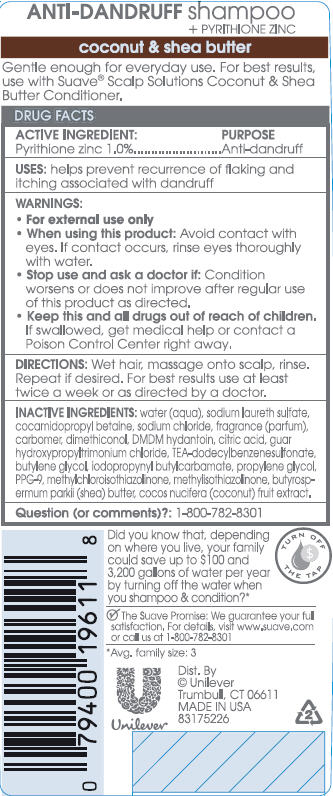 DRUG LABEL: Suave
NDC: 64942-1235 | Form: SHAMPOO
Manufacturer: Conopco Inc. d/b/a Unilever
Category: otc | Type: HUMAN OTC DRUG LABEL
Date: 20111222

ACTIVE INGREDIENTS: Pyrithione Zinc 1.0 mL/100 mL
INACTIVE INGREDIENTS: WATER; SODIUM LAURETH SULFATE; COCAMIDOPROPYL BETAINE; SODIUM CHLORIDE; CARBOMER HOMOPOLYMER TYPE C; BUTYLENE GLYCOL; DMDM HYDANTOIN; TEA-DODECYLBENZENESULFONATE; IODOPROPYNYL BUTYLCARBAMATE; CITRIC ACID MONOHYDRATE; PPG-9; METHYLCHLOROISOTHIAZOLINONE; METHYLISOTHIAZOLINONE; GUAR HYDROXYPROPYLTRIMONIUM CHLORIDE (1.7 SUBSTITUENTS PER SACCHARIDE); COCONUT; PROPYLENE GLYCOL; SHEA BUTTER

Suave Nourishing Coconut and Shea Butter Anti Dandruff Shampoo PDP and drug facts box

Active Ingredient

Pyrithione Zinc (1.0%)

Purpose
Antidandruff

INDICATIONS AND USAGE

Uses: helps prevent recurrence of flaking and itching associated with dandruff

Warnings
For external use only

When using this product: avoid contact with eyes. If contact occurs, rinse eyes thoroughly with water.

Stop use and ask a doctor if: Condition worsens or does not improve after regular use of this product as directed.

KEEP OUT OF REACH OF CHILDREN

Keep this and all drugs out of reach of children. If swallowed, get medical help or contact a Poison Control Center right away.

DOSAGE AND ADMINISTRATION

Directions: Wet hair, massage onto scalp, rinse. Repeat if desired. For best results use at least twice a week or as directed by a doctor.

Inactive Ingredients
Water
Sodium Laureth Sulfate
Cocamidopropyl Betaine
Sodium Chloride
Fragrance (Parfum)
Carbomer
Dimethiconol
DMDM Hydantoin
Citric Acid
Guar Hydroxypropyltrimonium Chloride
TEA-Dodecylbenzenesulfonate
Butylene Glycol
Iodopropynyl Butylcarbamate
Propylene Glycol
PPG-9
Methylchloroisothiazolinone
Methylisothiazolinone
Butyrospermum Parkii (Shea) Butter
Cocos Nucifera (Coconut) Fruit Extract

QUESTIONS

Question (or comments)?: 1-800-782-8301

PACKAGE LABEL

PDP front

PACKAGE LABEL

back